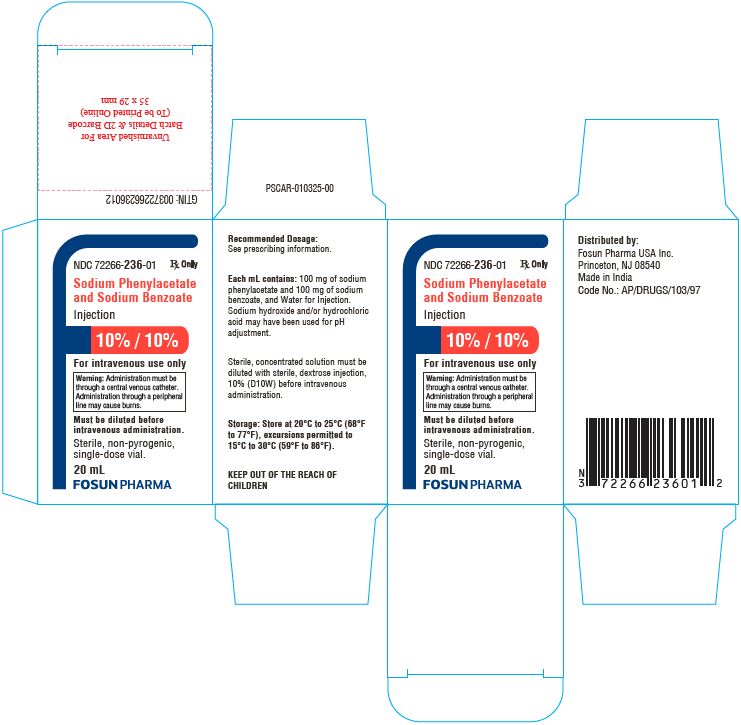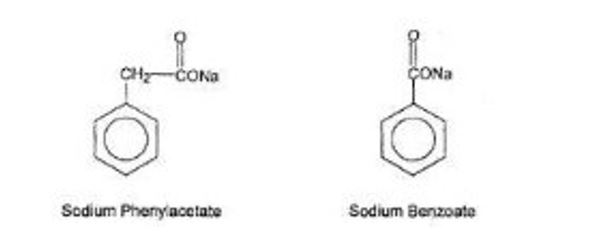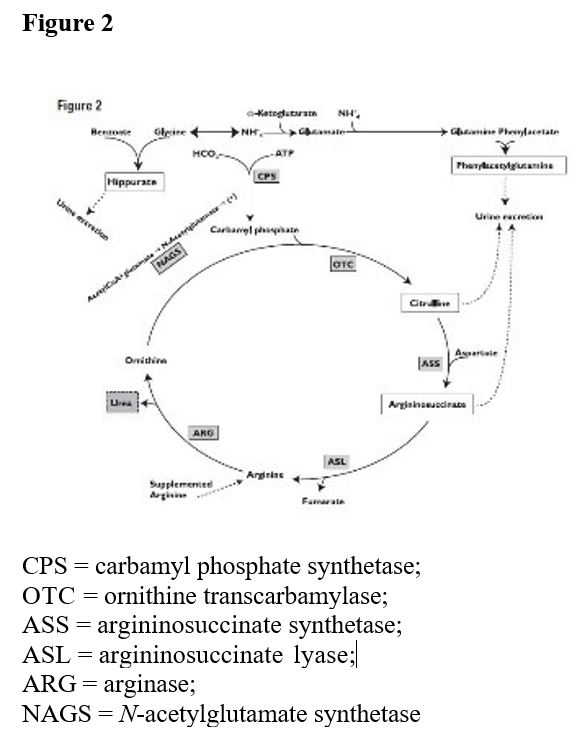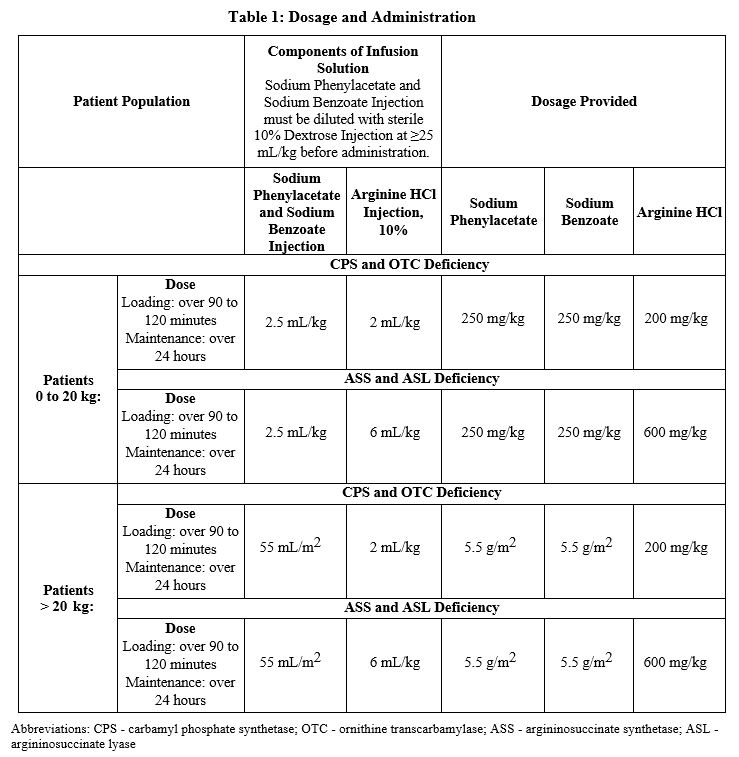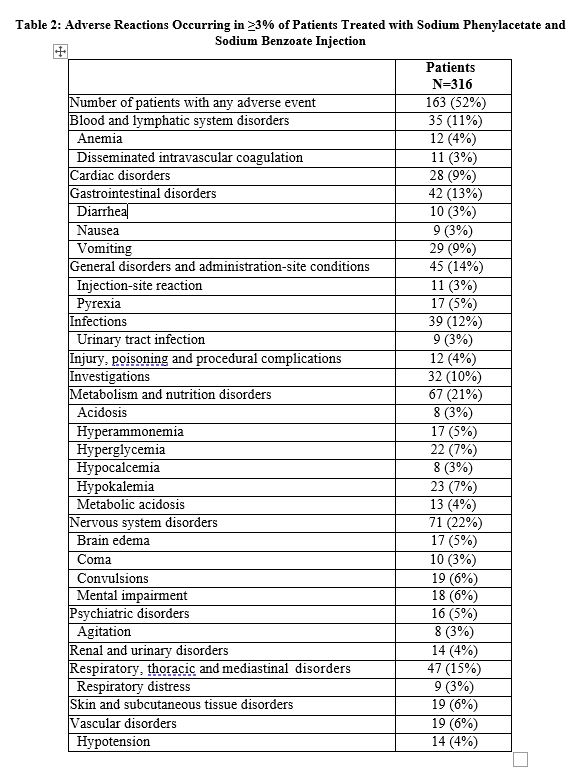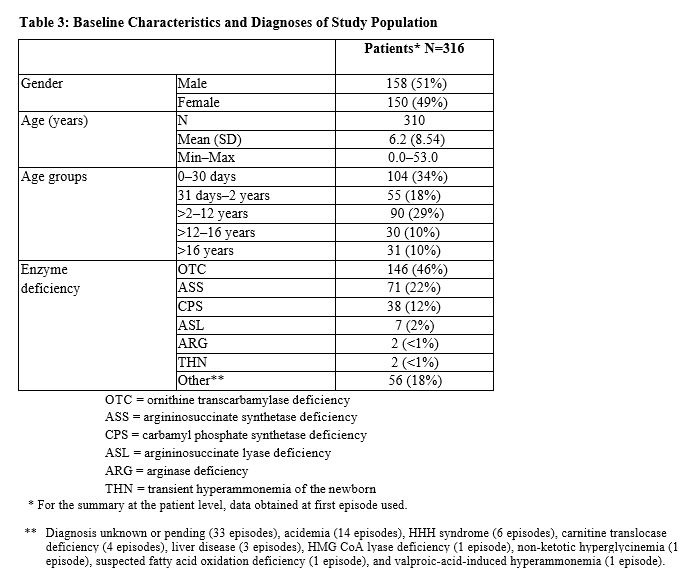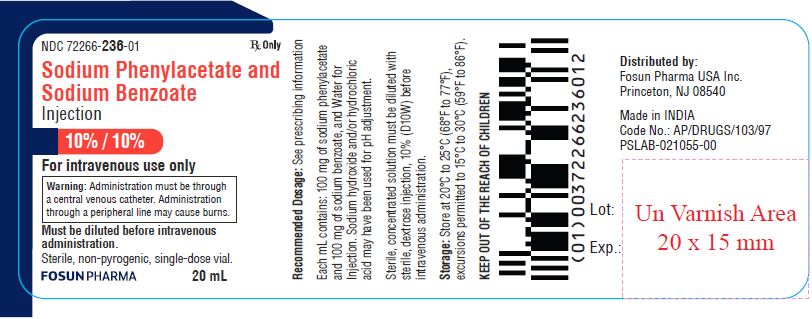 DRUG LABEL: Sodium Phenylacetate and Sodium Benzoate
NDC: 72266-236 | Form: INJECTION
Manufacturer: FOSUN PHARMA USA INC
Category: prescription | Type: HUMAN PRESCRIPTION DRUG LABEL
Date: 20240509

ACTIVE INGREDIENTS: SODIUM PHENYLACETATE 100 mg/1 mL; SODIUM BENZOATE 100 mg/1 mL
INACTIVE INGREDIENTS: SODIUM HYDROXIDE; HYDROCHLORIC ACID; WATER

HIGHLIGHTS OF PRESCRIBING INFORMATION

These highlights do not include all the information needed to use SODIUM PHENYLACETATE AND SODIUM BENZOATE INJECTION safely and effectively. See full prescribing information for SODIUM PHENYLACETATE AND SODIUM BENZOATE INJECTION.
SODIUM PHENYLACETATE AND SODIUM BENZOATE injection, for intravenous use
Initial U.S. Approval: 1987

1 INDICATIONS AND USAGE

Sodium Phenylacetate and Sodium Benzoate Injection is a nitrogen binding agent indicated as adjunctive therapy for the treatment of acute hyperammonemia and associated encephalopathy in pediatric and adult patients with deficiencies in enzymes of the urea cycle.

2 DOSAGE AND ADMINISTRATION

- Sodium Phenylacetate and Sodium Benzoate Injection must be diluted with sterile 10% Dextrose Injection (D10W) before administration. Administration must be through a central venous catheter. Administration through a peripheral line may cause burns. (2)

- Sodium Phenylacetate and Sodium Benzoate Injection is administered intravenously as a loading dose infusion administered over 90 to 120 minutes, followed by an equivalent maintenance dose infusion administered over 24 hours. (2)

- See Full Prescribing Information for complete dosing recommendations.

3 DOSAGE FORMS AND STRENGTHS

Injection: 10% per 10% sterile, concentrated, aqueous solution of sodium phenylacetate and sodium benzoate.

4 CONTRAINDICATIONS

None.

5 WARNINGS AND PRECAUTIONS

- Decreased Potassium Levels: Plasma potassium levels should be carefully monitored and appropriate treatment given when necessary. (5.1)

- Conditions Associated with Fluid Overload: Sodium Phenylacetate and Sodium Benzoate Injection contains 30.5 mg of sodium per mL of undiluted product. Caution should be used if Sodium Phenylacetate and Sodium Benzoate Injection is administered to patients with congestive heart failure, severe renal insufficiency, or with conditions in which there is sodium retention with edema. (5.2)

- Extravasation: Extravasation of Sodium Phenylacetate and Sodium Benzoate Injection into the perivenous tissues during high flow bolus infusion may lead to skin necrosis, especially in infants. The infusion site must be monitored closely for possible tissue infiltration during drug administration. (5.3)

- Neurotoxicity of Phenylacetate: Because of prolonged plasma levels achieved by phenylacetate in pharmacokinetic studies, repeat loading doses should not be administered. Additionally, neurotoxicity related to phenylacetate has been reported in cancer patients. Monitor patients for symptoms of acute neurotoxicity. (5.4)

- Hyperventilation and Metabolic Acidosis: Sodium Phenylacetate and Sodium Benzoate Injection may cause side effects typically associated with salicylate overdose, such as hyperventilation and metabolic acidosis. Monitor patient blood chemistry profiles and perform frequent blood pH and pCO2 measurements. (5.5)

6 ADVERSE REACTIONS

The most frequently reported adverse reactions (incidence ≥6%) are vomiting, hyperglycemia, hypokalemia, convulsions, and mental impairment

To report SUSPECTED ADVERSE REACTIONS, contact Fosun Pharma USA Inc. at 1-866-611-3762 or FDA at 1-800-FDA-1088 or www.fda.gov/medwatch.

7 DRUG INTERACTIONS

- Some antibiotics such as penicillin may affect the overall disposition of the infused drug. (7)
- Probenecid may affect renal excretion of phenylacetylglutamine and hippurate. (7)
- Valproic acid given to patients with urea cycle disorders may exacerbate their condition and antagonize the efficacy of Sodium Phenylacetate and Sodium Benzoate Injection through inhibition of the synthesis of N-acetylglutamate, a co-factor for carbamyl phosphate synthetase. (7)
- Use of corticosteroids may cause the breakdown of body protein and potentially increase plasma ammonia levels in patients with impaired ability to form urea. (7)

FULL PRESCRIBING INFORMATION

1 INDICATIONS AND USAGE

Sodium Phenylacetate and Sodium Benzoate Injection is indicated as adjunctive therapy in pediatric and adult patients for the treatment of acute hyperammonemia and associated encephalopathy in patients with deficiencies in enzymes of the urea cycle. During acute hyperammonemic episodes, arginine supplementation, caloric supplementation, dietary protein restriction, hemodialysis, and other ammonia lowering therapies should be considered [ see Warnings and Precautions (5)].

2 DOSAGE AND ADMINISTRATION

2.1 Recommended Dosage

Sodium Phenylacetate and Sodium Benzoate Injection must be diluted with sterile 10% Dextrose Injection (D10W) before administration. The dilution and dosage of Sodium Phenylacetate and Sodium Benzoate Injection are determined by weight for neonates, infants and young children, and by body surface area for larger patients, including older children, adolescents, and adults (Table 1).

2.2 Administration

Sodium Phenylacetate and Sodium Benzoate Injection is a concentrated solution and must be diluted before intravenous administration via a central venous catheter. Administration through a peripheral intravenous catheter may cause burns. Sodium Phenylacetate and Sodium Benzoate Injection may not be administered by any other route.

Sodium Phenylacetate and Sodium Benzoate Injection should be administered as a loading dose infusion over 90 to 120 minutes, followed by the same dose repeated as a maintenance infusion administered over 24 hours. Because of prolonged plasma levels achieved by phenylacetate in pharmacokinetic studies, repeat loading doses of Sodium Phenylacetate and Sodium Benzoate Injection should not be administered. Maintenance infusions may be continued until elevated plasma ammonia levels have been normalized or the patient can tolerate oral nutrition and medications. An antiemetic may be administered during Sodium Phenylacetate and Sodium Benzoate Injection infusion to aid control of infusion-associated nausea and vomiting. Administration of analogous oral drugs, such as sodium phenylbutyrate, should be terminated prior to Sodium Phenylacetate and Sodium Benzoate Injection infusion.

Sodium Phenylacetate and Sodium Benzoate Injection infusion should be started as soon as the diagnosis of hyperammonemia is made. Treatment of hyperammonemia also requires caloric supplementation and restriction of dietary protein. Non-protein calories should be supplied principally as glucose (8 to 10 mg/kg/min) with an intravenous fat emulsion added. Attempts should be made to maintain a caloric intake of greater than 80 kcal/kg/day. During and after infusion of Sodium Phenylacetate and Sodium Benzoate Injection, ongoing monitoring of the following clinical laboratory values is crucial: plasma ammonia, glutamine, quantitative plasma amino acids, blood glucose, electrolytes, venous or arterial blood gases, AST and ALT. On-going monitoring of the following clinical responses is also crucial to assess patient response to treatment: neurological status, Glasgow Coma Scale, tachypnea, CT or MRI scan or fundoscopic evidence of cerebral edema, and/or of gray matter and white matter damage. Hemodialysis should be considered in patients with severe hyperammonemia or who are not responsive to Sodium Phenylacetate and Sodium Benzoate Injection administration [ see Warnings and Precautions (5.1)]. In the non-neonatal study patient population treated with Sodium Phenylacetate and Sodium Benzoate Injection, dialysis was required in 13% of hyperammonemic episodes. Standard hemodialysis was the most frequently used dialysis method. High levels of ammonia can be reduced quickly when Sodium Phenylacetate and Sodium Benzoate Injection is used with hemodialysis, as the ammonia-scavenging of Sodium Phenylacetate and Sodium Benzoate Injection suppresses the production of ammonia from catabolism of endogenous protein and hemodialysis eliminates the ammonia and ammonia conjugates.

Sodium Phenylacetate and Sodium Benzoate Injection solutions are physically and chemically stable for up to 24 hours at room temperature and room lighting conditions. No compatibility information is presently available for Sodium Phenylacetate and Sodium Benzoate Injection infusion solutions except for Arginine HCl Injection, 10%, which may be mixed in the same container as Sodium Phenylacetate and Sodium Benzoate Injection. Other infusion solutions and drug products should not be administered together with Sodium Phenylacetate and Sodium Benzoate Injection infusion solution. Sodium Phenylacetate and Sodium Benzoate Injection solutions may be prepared in glass and PVC containers.

Arginine Administration

Intravenous arginine is an essential component of therapy for patients with carbamyl phosphate synthetase (CPS), ornithine transcarbamylase (OTC), argininosuccinate synthetase (ASS), or argininosuccinate lyase (ASL) deficiency. Because hyperchloremic acidosis may develop after high- dose arginine hydrochloride administration, chloride and bicarbonate levels should be monitored and appropriate amounts of bicarbonate administered.

In hyperammonemic infants with suspected, but unconfirmed urea cycle disorders, intravenous arginine should be given (6 mL/kg of Arginine HCl Injection 10%, over 90 minutes followed by the same dose given as a maintenance infusion over 24 hours). If deficiencies of ASS or ASL are excluded as diagnostic possibilities, the intravenous dose of Arginine HCl should be reduced to 2 mL/kg/day Arginine HCl Injection 10%.

Converting to Oral Treatment

Once elevated ammonia levels have been reduced to the normal range, oral therapy, such as sodium phenylbutyrate, dietary management and maintenance protein restrictions should be started or reinitiated.

3 DOSAGE FORMS AND STRENGTHS

Sodium Phenylacetate and Sodium Benzoate Injection 10% per 10% is a sterile, clear and almost colorless concentrated, aqueous solution of sodium phenylacetate and sodium benzoate.

4 CONTRAINDICATIONS

None

5 WARNINGS AND PRECAUTIONS

5.1 Decreased Potassium Levels

Because urine potassium loss is enhanced by the excretion of the non-reabsorbable anions, phenylacetylglutamine and hippurate, plasma potassium levels should be carefully monitored and appropriate treatment given when necessary.

5.2 Conditions Associated with Fluid Overload

Sodium Phenylacetate and Sodium Benzoate Injection contains 30.5 mg of sodium per mL of undiluted product. Thus, Sodium Phenylacetate and Sodium Benzoate Injection should be used with great care, if at all, in patients with congestive heart failure or severe renal insufficiency, and in clinical states in which there is sodium retention with edema. Discontinue administration of Sodium Phenylacetate and Sodium Benzoate Injection, evaluate the patient, and institute appropriate therapeutic countermeasures if an adverse event occurs.

5.3 Extravasation

Administration must be through a central venous catheter. Administration through a peripheral line may cause burns. Bolus infusion flow rates are relatively high, especially for infants [see Dosage and Administration (2)]. Extravasation of Sodium Phenylacetate and Sodium Benzoate Injection into the perivenous tissues may lead to skin necrosis. If extravasation is suspected, discontinue the infusion and resume at a different infusion site, if necessary. The infusion site must be monitored closely for possible infiltration during drug administration. Do not administer undiluted product.

5.4 Neurotoxicity of Phenylacetate

Because of prolonged plasma levels achieved by phenylacetate in pharmacokinetic studies, repeat loading doses of Sodium Phenylacetate and Sodium Benzoate Injection should not be administered. Additionally, neurotoxicity was reported in cancer patients receiving intravenous phenylacetate, 250 to 300 mg/kg/day for 14 days, repeated at 4-week intervals. Manifestations were predominantly somnolence, fatigue, and lightheadedness, with less frequent headaches, dysgeusia, hypoacusis, disorientation, impaired memory, and exacerbation of a pre- existing neuropathy. The acute onset of symptoms upon initiation of treatment and reversibility of symptoms when the phenylacetate was discontinued suggest a drug effect [ see Animal Toxicology and/or Pharmacology (13.2)].

5.5 Hyperventilation and Metabolic Acidosis

Due to structural similarities between phenylacetate and benzoate to salicylate, Sodium Phenylacetate and Sodium Benzoate Injection may cause side effects typically associated with salicylate overdose, such as hyperventilation and metabolic acidosis. Monitoring of blood chemistry profiles, blood pH andpCO2 should be performed.

6 ADVERSE REACTIONS

6.1 Clinical Trials Experience

Because clinical trials are conducted under widely varying conditions, adverse reaction rates observed in the clinical trials of a drug cannot be directly compared to rates in the clinical trials of another drug and may not reflect the rates observed in practice.

The safety data were obtained from 316 patients who received Sodium Phenylacetate and Sodium Benzoate Injection as emergency (rescue) or prospective treatment for hyperammonemia as part of an uncontrolled, open-label study. The study population included patients between the ages of 0 to 53 years with a mean (SD) of 6.2 (8.54) years; 51% were male and 49% were female who had the following diagnoses: OTC (46%), ASS (22%), CPS (12%), ASL (2%), ARG (<1%), THN (<1%), and other (18%).

Adverse reactions were reported with similar frequency in patients with OTC, ASS, CPS, and diagnoses categorized as "other." Nervous system disorders were more frequent in patients with OTC and CPS, compared with patients with ASS and patients with "other" diagnoses. Convulsions and mental impairment were reported in patients with OTC and CPS. These observations are consistent with literature reports that patients with enzyme deficiencies occurring earlier in the urea cycle (i.e., OTC and CPS) tend to be more severely affected.

Adverse reactions profiles differed by age group. Patients ≤30 days of age had more blood and lymphatic system disorders and vascular disorders (specifically hypotension), while patients >30 days of age had more gastrointestinal disorders (specifically nausea, vomiting and diarrhea).

Less common adverse reactions (<3% of patients) that are characterized as severe are listed below by body system.

BLOOD AND LYMPHATIC SYSTEM DISORDERS: coagulopathy, pancytopenia, thrombocytopenia

CARDIAC DISORDERS: atrial rupture, bradycardia, cardiac or cardiopulmonary arrest/failure, cardiogenic shock, cardiomyopathy, pericardial effusion

EYE DISORDERS: blindness

GASTROINTESTINAL DISORDERS: abdominal distension, gastrointestinal hemorrhage

GENERAL DISORDERS AND ADMINISTRATION-SITE CONDITIONS: asthenia, brain death, chest pain, multiorgan failure, edema

HEPATOBILIARY DISORDERS: cholestasis, hepatic artery stenosis, hepatic failure/hepatotoxicity, jaundice

INFECTIONS AND INFESTATIONS: sepsis/septic shock

INJURY, POISONING AND PROCEDURAL COMPLICATIONS: brain herniation, subdural hematoma, overdose

INVESTIGATIONS: blood carbon dioxide changes, blood glucose changes, blood pH increased, cardiac output decreased, pCO2 changes, respiratory rate increased

METABOLISM AND NUTRITION DISORDERS: alkalosis, dehydration, fluid overload/retention, hypoglycemia, hyperkalemia, hypernatremia, alkalosis, tetany

NEOPLASMS BENIGN, MALIGNANT AND UNSPECIFIED: hemangioma acquired

NERVOUS SYSTEM DISORDERS: areflexia, ataxia, brain infarction, brain hemorrhage, cerebral atrophy, clonus, depressed level of consciousness, encephalopathy, nerve paralysis, intracranial pressure increased, subdural hematoma, tremor

PSYCHIATRIC DISORDERS: acute psychosis, aggression, confusional state, hallucinations

RENAL AND URINARY DISORDERS: anuria, renal failure, urinary retention

RESPIRATORY, THORACIC AND MEDIASTINAL DISORDERS: acute respiratory distress syndrome, dyspnea, hypercapnia, hyperventilation, Kussmaul respiration, pneumonia aspiration,

pneumothorax, pulmonary hemorrhage, pulmonary edema, respiratory acidosis or alkalosis, respiratory arrest/failure

SKIN AND SUBCUTANEOUS TISSUE DISORDERS: alopecia, blister, pruritus generalized, rash, urticaria

VASCULAR DISORDERS: flushing, hemorrhage, hypertension, phlebothrombosis/thrombosis

7 DRUG INTERACTIONS

Formal drug interaction studies have not been performed with Sodium Phenylacetate and Sodium Benzoate Injection.

Some antibiotics such as penicillin may compete with phenylacetylglutamine and hippurate for active secretion by renal tubules, which may affect the overall disposition of the infused drug.

Probenecid is known to inhibit the renal transport of many organic compounds, including aminohippuric acid, and may affect renal excretion of phenylacetylglutamine and hippurate.

There have been reports that valproic acid can induce hyperammonemia through inhibition of the synthesis of N-acetylglutamate, a co-factor for carbamyl phosphate synthetase. Therefore, administration of valproic acid to patients with urea cycle disorders may exacerbate their condition and antagonize the efficacy of Sodium Phenylacetate and Sodium Benzoate Injection.

Use of corticosteroids may cause a protein catabolic state and, thereby, potentially increase plasma ammonia levels in patients with impaired ability to form urea.

8 USE IN SPECIFIC POPULATIONS

8.1 Pregnancy

Risk Summary

Available data on the combination use of sodium phenylacetate and sodium benzoate in pregnant women are insufficient to identify a drug associated risk of major birth defects, miscarriage or adverse maternal or fetal outcomes. Animal reproduction studies have not been conducted with Sodium Phenylacetate and Sodium Benzoate Injection.

The estimated background risk of major birth defects and miscarriage for the indicated population is unknown. All pregnancies have a background risk of birth defect, loss or other adverse outcomes. In the U.S. general population, the estimated background risk of major birth defects and miscarriage in clinically recognized pregnancies is 2 to 5% and 15 to 20%, respectively.

8.2 Lactation

Risk Summary

There are no data on the presence of sodium phenylacetate, sodium benzoate in either human or animal milk, the effects on the breastfed infant, or the effects on milk production. The developmental and health benefits of breastfeeding should be considered along with the mother's clinical need for Sodium Phenylacetate and Sodium Benzoate Injection and any potential adverse effects on the breastfed infant from Sodium Phenylacetate and Sodium Benzoate Injection or from the underlying maternal condition.

8.4 Pediatric Use

Sodium Phenylacetate and Sodium Benzoate Injection has been used as a treatment for acute hyperammonemia in pediatric patients including patients in the early neonatal period [ see Dosage and Administration (2)].

8.5 Geriatric Use

Clinical studies of Sodium Phenylacetate and Sodium Benzoate Injection did not include any patients aged 65 and over to determine whether they respond differently from younger patients. Urea cycle disorders are presently diseases of the pediatric and younger adult populations. No pharmacokinetic studies of Sodium Phenylacetate and Sodium Benzoate Injection have been performed in geriatric patients. In general, dose selection for an elderly patient should be cautious, usually starting at the low end of the dosing range, reflecting the greater frequency of decreased hepatic, renal, or cardiac function, and concomitant disease or other drug therapy in this patient population.

8.6 Gender

Pharmacokinetic parameters of Sodium Phenylacetate and Sodium Benzoate Injection were compared in healthy males and females. Bioavailability of both benzoate and phenylacetate was slightly higher in females than in males. However, conclusions cannot be drawn due to the limited number of subjects in this study.

8.7 Hepatic Insufficiency

Limited information is available on the metabolism and excretion of sodium phenylacetate and sodium benzoate in patients with impaired hepatic function. However, metabolic conjugation of sodium phenylacetate and sodium benzoate is known to take place in the liver and kidney. Therefore, caution should be used in administering Sodium Phenylacetate and Sodium Benzoate Injection to patients with hepatic insufficiency.

8.8 Renal Impairment

The drug metabolites of Sodium Phenylacetate and Sodium Benzoate Injection (phenylacetylglutamine and hippurate) and subsequently ammonia are primarily excreted by the kidney. Therefore, use caution and closely monitor patients with impaired renal function who receive Sodium Phenylacetate and Sodium Benzoate Injection.

10 OVERDOSAGE

Overdosage has been reported during Sodium Phenylacetate and Sodium Benzoate Injection treatment in urea cycle-deficient patients. All patients in the uncontrolled open-label study were to be treated with the same dose of Sodium Phenylacetate and Sodium Benzoate Injection. However, some patients received more than the dose level specified in the protocol. In 16 of the 64 deaths, the patient received a known overdose of Sodium Phenylacetate and Sodium Benzoate Injection. Causes of death in these patients included cardiorespiratory failure/arrest (6 patients), hyperammonemia (3 patients), increased intracranial pressure (2 patients), pneumonitis with septic shock and coagulopathy (1 patient), error in dialysis procedure (1 patient), respiratory failure (1 patient), intractable hypotension and probable sepsis (1 patient), and unknown (1 patient). Additionally, other signs of intoxication may include obtundation (in the absence of hyperammonemia), hyperventilation, a severe compensated metabolic acidosis, perhaps with a respiratory component, large anion gap, hypernatremia and hyperosmolarity, progressive encephalopathy, cardiovascular collapse, and death.

In case of overdose of Sodium Phenylacetate and Sodium Benzoate Injection, discontinue the drug and institute appropriate emergency medical monitoring and procedures. In severe cases, the latter may include hemodialysis (procedure of choice) or peritoneal dialysis (when hemodialysis is unavailable

11 DESCRIPTION

Sodium Phenylacetate and Sodium Benzoate Injection 10% per 10% (a nitrogen binding agent) is a sterile, concentrated, aqueous solution of sodium phenylacetate and sodium benzoate. The pH of the solution is between 7.5 and 8.3. Sodium phenylacetate is a white to off-white powder. It is soluble in water. Sodium benzoate is a white to off-white and powder that is readily soluble in water.

Figure 1

Sodium Phenylacetate has a molecular weight of 158.14 and the molecular formula C8H5NaO2. Sodium benzoate has molecular weight of 144.10 and the molecular formula C7H5NaO2

Each mL of Sodium Phenylacetate and Sodium Benzoate Injection contains 100 mg of sodium phenylacetate and 100 mg of sodium benzoate, and Water for Injection. Sodium hydroxide and/or hydrochloric acid may have been used for pH adjustment.

Sodium Phenylacetate and Sodium Benzoate Injection is a sterile, concentrated solution intended for intravenous administration via a central catheter only after dilution [see Dosage and Administration (2)]

12 CLINICAL PHARMACOLOGY

12.1 Mechanism of Action

Urea cycle disorders can result from decreased activity of any of the following enzymes: N-acetylglutamate synthetase (NAGS), carbamyl phosphate synthetase (CPS), argininosuccinate synthetase (ASS), ornithine transcarbamylase (OTC), argininosuccinate lyase (ASL), or arginase (ARG).

Sodium phenylacetate and sodium benzoate are metabolically active compounds that can serve as alternatives to urea for the excretion of waste nitrogen. Figure 2 is a schematic illustrating how the components of Sodium Phenylacetate and Sodium Benzoate Injection, phenylacetate and benzoate, provide an alternative pathway for nitrogen disposal in patients without a fully functioning urea cycle. Phenylacetate conjugates with glutamine in the liver and kidneys to form phenylacetylglutamine, via acetylation. Phenylacetylglutamine is excreted by the kidneys via glomerular filtration and tubular secretion. The nitrogen content of phenylacetylglutamine per mole is identical to that of urea (both contain two moles of nitrogen). Two moles of nitrogen are removed per mole of phenylacetate when it is conjugated with glutamine. Similarly, preceded by acylation, benzoate conjugates with glycine to form hippuric acid, which is rapidly excreted by the kidneys by glomerular filtration and tubular secretion. One mole of hippuric acid contains one mole of waste nitrogen. Thus, one mole of nitrogen is removed per mole of benzoate when it is conjugated with glycine.

12.2 Pharmacodynamics

In patients with hyperammonemia due to deficiencies in enzymes of the urea cycle, Sodium Phenylacetate and Sodium Benzoate Injection has been shown to decrease elevated plasma ammonia levels. These effects are considered to be the result of reduction in nitrogen overload through glutamine and glycine scavenging by Sodium Phenylacetate and Sodium Benzoate Injection in combination with appropriate dietary and other supportive measures.

12.3 Pharmacokinetics

The pharmacokinetics of intravenously administered Sodium Phenylacetate and Sodium Benzoate Injection was characterized in healthy adult volunteers. Both benzoate and phenylacetate exhibited nonlinear kinetics. Following 90 minute intravenous infusion mean AUClast for benzoate was 20.3, 114.9, 564.6, 562.8, and 1599.1 mcg/mL following doses of 1, 2, 3.75, 4, and 5.5 g/m^2, respectively. The total clearance decreased from 5.19 to 3.62 L/h/m^2 at the 3.75 and 5.5 g/m^2 doses, respectively.

Similarly, phenylacetate exhibited nonlinear kinetics following the priming dose regimens. AUClast was 175.6, 713.8, 2040.6, 2181.6, and 3829.2 mcg·h/mL following doses of 1, 2, 3.75, 4, and 5.5 g/m^2, respectively. The total clearance decreased from 1.82 to 0.89 mcg·h/mL with increasing dose (3.75 and 4 g/m^2, respectively).

During the sequence of 90-minute priming infusion followed by a 24-hour maintenance infusion, phenylacetate was detected in the plasma at the end of infusion (Tmax of 2 hr at 3.75 g/m^2) whereas, benzoate concentrations declined rapidly (Tmax of 1.5 hr at 3.75 g/m^2) and were undetectable at 14 and 26 hours following the 3.75 and 4 g/m^2 dose, respectively.

A difference in the metabolic rates for phenylacetate and benzoate was noted. The formation of hippurate from benzoate occurred more rapidly than that of phenylacetylglutamine from phenylacetate, and the rate of elimination for hippurate appeared to be more rapid than that for phenylacetylglutamine.

Pharmacokinetic observations have also been reported from twelve episodes of hyperammonemic encephalopathy in seven children diagnosed (age 3 to 26 months) with urea cycle disorders who had been administered Sodium Phenylacetate and Sodium Benzoate Injection intravenously. These data showed peak plasma levels of phenylacetate and benzoate at approximately the same times as were observed in healthy adults. As in healthy adults, the plasma levels of phenylacetate were higher than benzoate and were present for a longer time.

The pharmacokinetics of intravenous phenylacetate have been reported following administration to adult patients with advanced solid tumors. The decline in serum phenylacetate concentrations following a loading infusion of 150 mg/kg was consistent with saturable enzyme kinetics. Ninety-nine percent of administered phenylacetate was excreted as phenylacetylglutamine.

13 NONCLINICAL TOXICOLOGY

13.1 Carcinogenesis, Mutagenesis, Impairment of Fertility

Long-term studies in animals have not been performed to evaluate the carcinogenic potential of Sodium Phenylacetate and Sodium Benzoate Injection. Studies to evaluate the possible impairment of fertility or mutagenic potential of Sodium Phenylacetate and Sodium Benzoate Injection have not been performed. Results indicate that sodium benzoate is not mutagenic or carcinogenic and does not impair fertility.

13.2 Animal Toxicology and/or Pharmacology

In animal studies, subcutaneous administration to rat pups of 190 to 474 mg/kg of phenylacetate caused decreased proliferation and increased loss of neurons, and reduced central nervous system (CNS) myelin. Cerebral synapse maturation was retarded, and the number of functioning nerve terminals in the cerebrum was reduced, which resulted in impaired brain growth. Pregnant rats were given phenylacetate at 3.5 µmol/g/day subcutaneously from gestation day 7 through normal delivery. Prenatal exposure of rat pups to phenylacetate produced lesions in layer 5 cortical pyramidal cells; dendritic spines were longer and thinner than normal and reduced in number.

14 CLINICAL STUDIES

The efficacy of Sodium Phenylacetate and Sodium Benzoate Injection in improving patient survival of acute hyperammonemic episodes was demonstrated in an analysis of 316 patients (1,045 episodes of hospitalization) treated between 1981 and 2003.

The demographic characteristics and diagnoses of the patient population are shown in Table 3.

On admission to the hospital, patients with hyperammonemia and a suspected or confirmed urea cycle disorder (UCD) diagnosis were treated with a bolus dose of 0.25 g/kg (or 5.5 g/m^2) sodium phenylacetate + 0.25 g/kg (or 5.5 g/m^2) sodium benzoate over a period of 90 minutes to 6 hours, depending on the specific UCD. Infusions also contained arginine; the dose of arginine depended on the specific UCD. After completion of the bolus dose, maintenance infusions of the same dose over 24 hours were continued until the patient was no longer hyperammonemic or oral therapy could be tolerated. The mean (SD) duration of treatment was 4.6 (6.45) days per episode, and ranged from 1 to 72 days.

Survival was substantially improved after Sodium Phenylacetate and Sodium Benzoate Injection treatment compared with historical values (estimated 14% 1-year survival rate with dietary therapy alone) and with dialysis (estimated 43% survival of acute hyperammonemia).

Eighty percent of patients (252 of 316) survived their last episode. Of the 64 patients who died, 53 (83%) died during their first hyperammonemic episode. Of the 104 neonates (<30d) treated with Sodium Phenylacetate and Sodium Benzoate Injection, 34 (33%) died during the first hyperammonemic episode.

Ammonia levels decreased from very high levels (>4 times the upper limit of normal [ULN]) to lower levels in 91% of episodes after treatment. In patients responding to therapy, mean ammonia concentrations decreased from 200.9 µmol/L at hour zero to 101.6 µmol/L within four hours of initiation of Sodium Phenylacetate and Sodium Benzoate Injection therapy and were maintained. Hemodialysis is recommended for those patients whose plasma ammonia levels fail to fall below 150 µmol/L or by more than 40% within 4 to 8 hours after receiving Sodium Phenylacetate and Sodium Benzoate Injection. A shift from high (≤4 times ULN) to very high (>4 times ULN) levels was observed in only 4% of the episodes.

Overall, investigators rated neurological status as improved, much improved, or the same in 93% of episodes, and overall status in response to treatment as improved, much improved, or the same in 97% of episodes. Recovery from coma was observed in 97% of episodes where coma was present at admission (111 of 114 episodes).

16 HOW SUPPLIED/STORAGE AND HANDLING

Sodium Phenylacetate and Sodium Benzoate Injection 10% per 10% is clear and almost colorless solution supplied in a sterile, non-pyrogenic, single-dose glass vial.

NDC 72266-236-01 single-dose vial containing 20 mL of Sodium Phenylacetate and Sodium Benzoate Injection 10% per 10%.

Storage: Store at 20°C to 25°C (77°F); excursions permitted to 15°C to 30°C (59°F to 86°F).

17 PATIENT COUNSELING INFORMATION

Physicians should advise patients and caregivers about the following for safe use of Sodium Phenylacetate and Sodium Benzoate Injection:

- When plasma ammonia levels have normalized, dietary protein intake can usually be increased with the goal of unrestricted protein intake.
- The most common adverse reactions are vomiting, hyperglycemia, hypokalemia, convulsions, and mental impairment.
- Generally BUPHENYL is stopped during the time Sodium Phenylacetate and Sodium Benzoate Injection is used.

Distributed by:

Fosun Pharma USA Inc.
Princeton, NJ 08540
Made in India

PSLEA-020543-00

Principal Display Panel

Carton

Vial